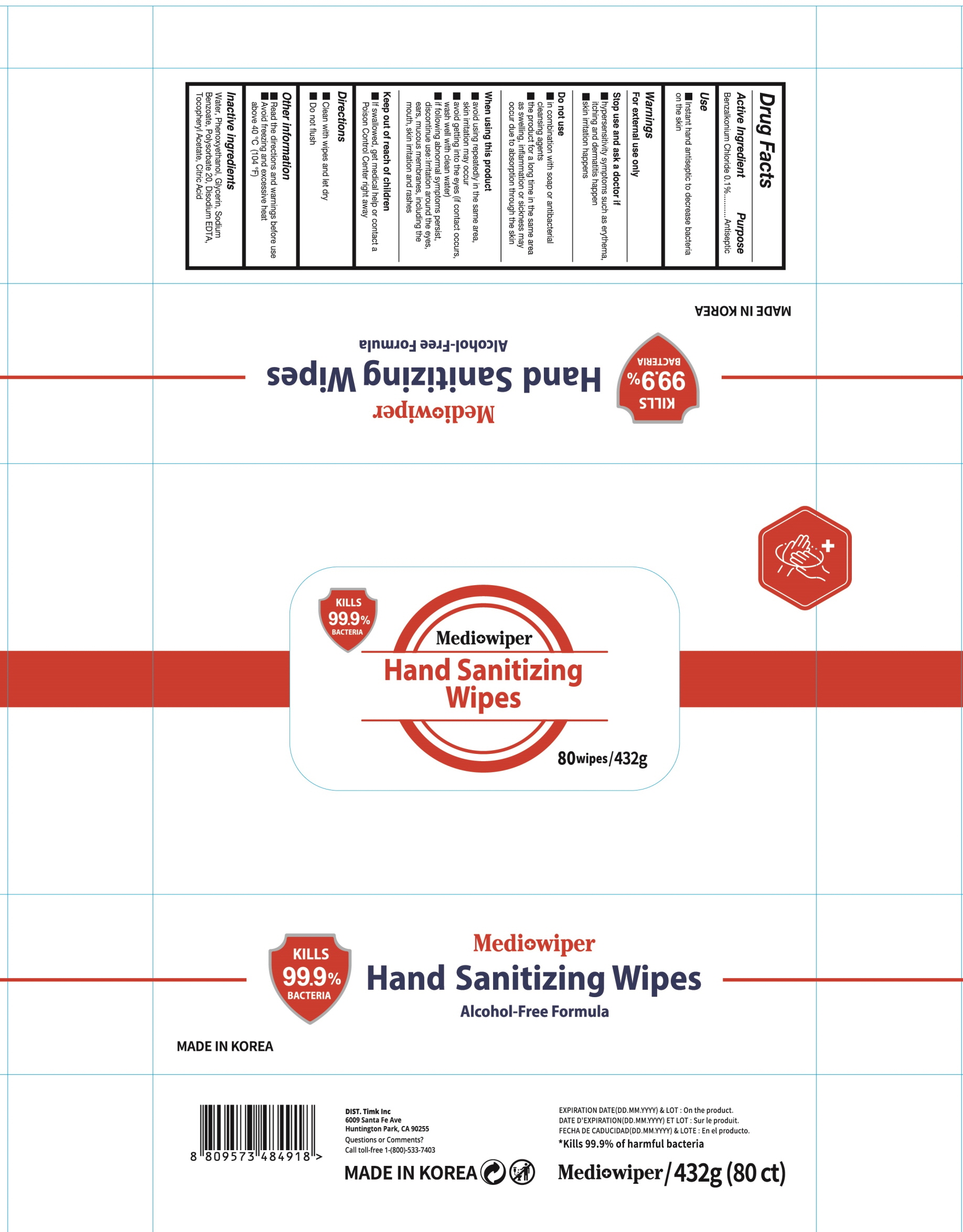 DRUG LABEL: Medi wiper Hand Sanitizing Wipes
NDC: 83930-010 | Form: LIQUID
Manufacturer: TIMK, INC.
Category: otc | Type: HUMAN OTC DRUG LABEL
Date: 20240112

ACTIVE INGREDIENTS: Benzalkonium Chloride 0.1 g/100 g
INACTIVE INGREDIENTS: Water; Phenoxyethanol; Glycerin; Sodium Benzoate; Polysorbate 20; EDETATE DISODIUM ANHYDROUS; .ALPHA.-TOCOPHEROL ACETATE; CITRIC ACID MONOHYDRATE

ACTIVE INGREDIENT

Benzalkonium Chloride 0.1%

Inactive ingredients

Water, Phenoxyethanol, Glycerin, Sodium Benzoate, Polysorbate20, Disodium EDTA, Tocopheryl Acetate, Citric Acid

PURPOSE

Antiseptic

WARNINGS

For external use only
------------------------------------------------------------------------------
Stop use and ask a doctor if
■ hypersensitivity symptoms such as erythema, itching and dermatitis happen
■ skin irritation happens
------------------------------------------------------------------------------
Do not use
■ in combination with soap or antibacterial cleansing agents
■ the product for a long time in the same area as swelling, inflammation or sickness may occur due to absorption through the skin
-------------------------------------------------------------------------------
When using this product
■ aviod using repeatedly in the same area, skin irritation may occur
■ avoid getting into the eyes (if contact occurs, wash well with clean water)
■ if following abnormal symptoms persist, discontinue use :
Irritation around the eyes, ears, mucous membranes, including the mouth, skin irritation and rashes
-------------------------------------------------------------------------------
Keep out of reach of children
■ If swallowed, get medical help or contact a Poison Control Center right away

KEEP OUT OF REACH OF CHILDREN

■ If swallowed, get medical help or contact a Poison Control Center right away

Uses

Instant hand antiseptic to decrease bacteria on the skin

Directions

■ Clean with wipes and let dry
■ Do not flush

Other Information

■ Read the directions and warnings before use
■ Avoid freezing and excessive heat above 40 degree C (104 degree F)